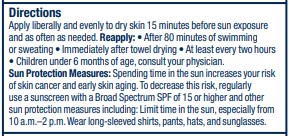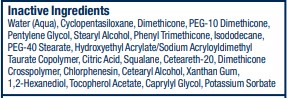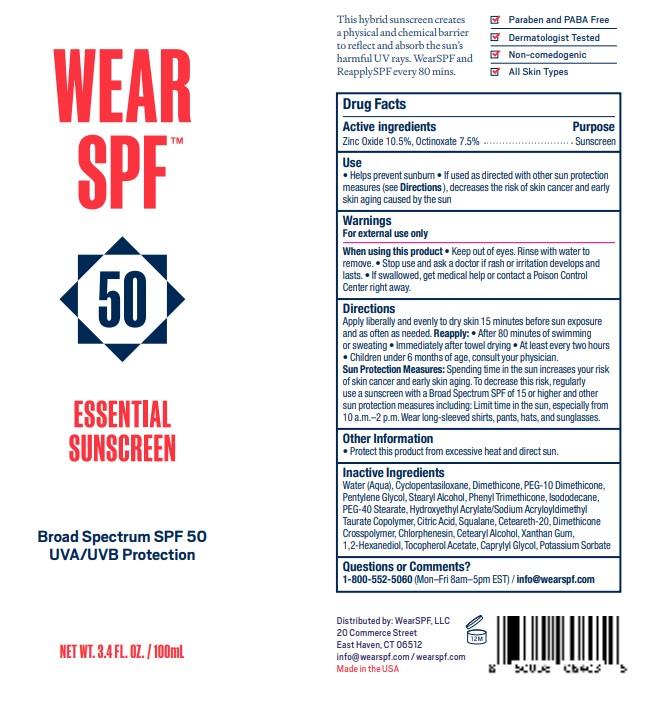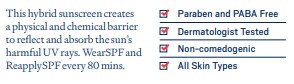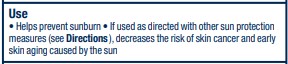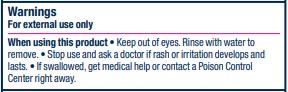 DRUG LABEL: Essential Sunscreen SPF50
NDC: 57577-571 | Form: LOTION
Manufacturer: Milbar Laboratories
Category: otc | Type: HUMAN OTC DRUG LABEL
Date: 20240729

ACTIVE INGREDIENTS: ZINC OXIDE 11.508 g/100 mL; OCTINOXATE 8.22 g/100 mL
INACTIVE INGREDIENTS: CAPRYLYL GLYCOL; CHLORPHENESIN; XANTHAN GUM; SQUALANE; ISODODECANE; POLYOXYL 20 CETOSTEARYL ETHER; HYDROXYETHYL ACRYLATE/SODIUM ACRYLOYLDIMETHYL TAURATE COPOLYMER (100000 MPA.S AT 1.5%); 1,2-HEXANEDIOL; WATER; PENTYLENE GLYCOL; CITRIC ACID MONOHYDRATE; CETOSTEARYL ALCOHOL; PEG-40 MONOSTEARATE; CYCLOMETHICONE 5; DIMETHICONE; PHENYL TRIMETHICONE; POTASSIUM SORBATE; STEARYL ALCOHOL; DIMETHICONE CROSSPOLYMER; .ALPHA.-TOCOPHEROL ACETATE; PEG-10 DIMETHICONE (220 CST)

Essential Sunscreen SPF50